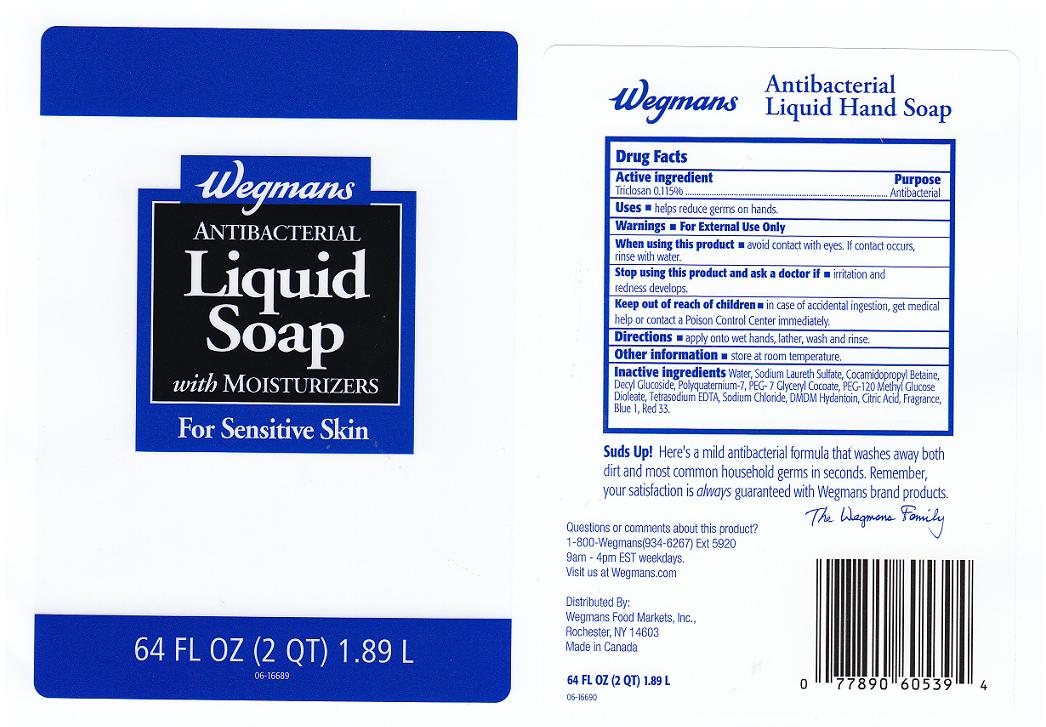 DRUG LABEL: ANTIBACTERIAL 
NDC: 47124-720 | Form: LIQUID
Manufacturer: WEGMANS FOOD MARKETS INC
Category: otc | Type: HUMAN OTC DRUG LABEL
Date: 20110615

ACTIVE INGREDIENTS: TRICLOSAN 0.115 mL/100 mL
INACTIVE INGREDIENTS: WATER; SODIUM LAURETH SULFATE; COCAMIDOPROPYL BETAINE; DECYL GLUCOSIDE; POLYQUATERNIUM-7 (70/30 ACRYLAMIDE/DADMAC; 1600 KD); PEG-7 GLYCERYL COCOATE; PEG-120 METHYL GLUCOSE DIOLEATE; EDETATE SODIUM; SODIUM CHLORIDE; DMDM HYDANTOIN; CITRIC ACID MONOHYDRATE; FD&C BLUE NO. 1; D&C RED NO. 33

DRUG FACTS

ACTIVE INGREDIENT

TRICLOSAN 0.115%

PURPOSE

ANTIBACTERIAL

USES

HELPS REDUCE GERMS ON HANDS.

WARNINGS

FOR EXTERNAL USE ONLY.

WHEN USING THIS PRODUCT

AVOID CONTACT WITH EYES. IF CONTACT OCCURS, RINSE WITH WATER.

STOP USING THIS PRODUCT AND ASK A DOCTOR IF

IRRITATION AND REDNESS DEVELOPS.

KEEP OUT OF REACH OF CHILDREN

IN CASE OF ACCIDENTAL INGESTION, GET MEDICAL HELP OR CONTACT A POISON CONTROL CENTER IMMEDIATELY.

DIRECTIONS

APPLY ONTO WET HANDS, LATHER, WASH AND RINSE.

OTHER INFORMATION

STORE AT ROOM TEMPERATURE.

INACTIVE INGREDIENTS

WATER, SODIUM LAURETH SULFATE, COCAMIDOPROPYL BETAINE, DECYL GLUCOSIDE, POLYQUATERNIUM-7, PEG- 7 GLYCERYL COCOATE, PEG-120 METHYL GLUCOSE DIOLEATE, TETRASODIUM EDTA, SODIUM CHLORIDE, DMDM HYDANTOIN,CITRIC ACID, FRAGRANCE, BLUE 1 (CI 42090), RED 33 (CI 17200).